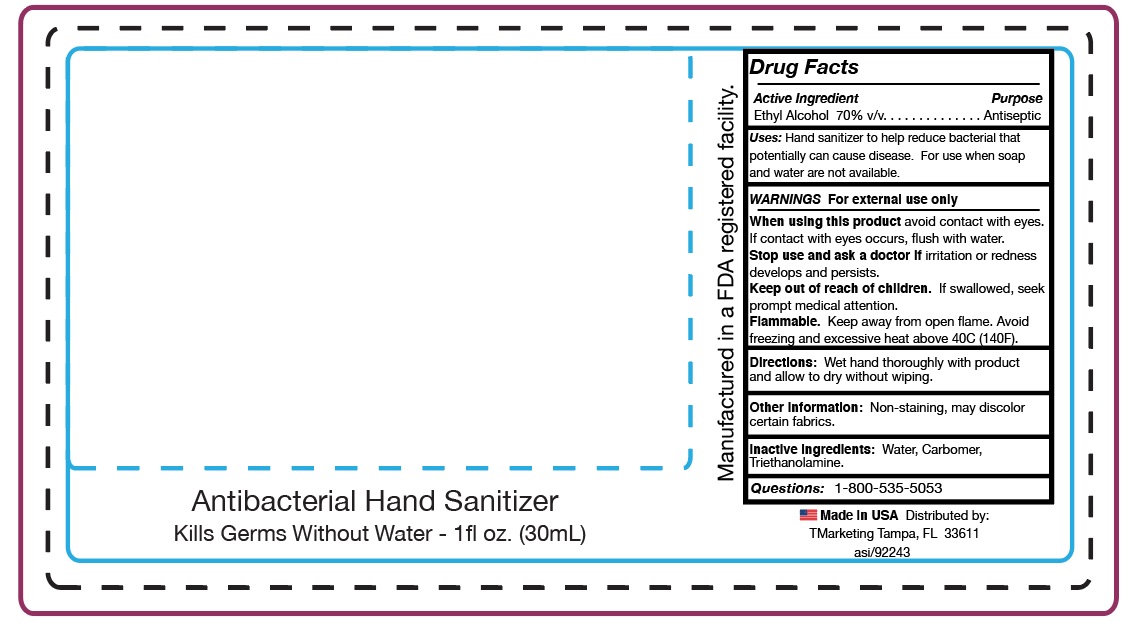 DRUG LABEL: Hand Sanitizer
NDC: 58418-116 | Form: GEL
Manufacturer: Tropical Enterprises International, Inc.
Category: otc | Type: HUMAN OTC DRUG LABEL
Date: 20200203

ACTIVE INGREDIENTS: ALCOHOL 20.4 mL/30 mL
INACTIVE INGREDIENTS: TROLAMINE; CARBOMER 1342; WATER

Formula #1000-B-Bulk gel - 70% ethyl alcohol hand sanitizer

ACTIVE INGREDIENT

Ethyl Alcohol 70% v/v

DOSAGE AND ADMINISTRATION

Directions: Wet hands thoroughly with product and allow to dry without wiping.

INACTIVE INGREDIENT

InActive Ingredients: Water, Carbomer, Triethanolamine

INDICATIONS AND USAGE

Use Hand Sanitizer to help reduce bacteria that potentially can cause disease.

For use when soap and water are not available.

Use: updated

Use Hand Sanitizer to help reduce bacteria that potentially can cause disease.

For use when soap and water are not available.

Keep out of reach of children. If swallowed, seek prompt medical attention.

OTC PURPOSE

Purpose... Antiseptic

WARNING

WARNINGS: For external use only

When using this product avoid contact with eyes. If contact with eyes occurs, flush with water.

Stop use and ask a doctor if irritation or redness develops and persists. If swallowed, seek prompt medical attention.

Other information: Non-staining, may discolor certain fabrics.

SAFE HANDLING WARNING

Flammable: Keep away from open flame.

Avoid freezing and excessive heat above 40C (104F).